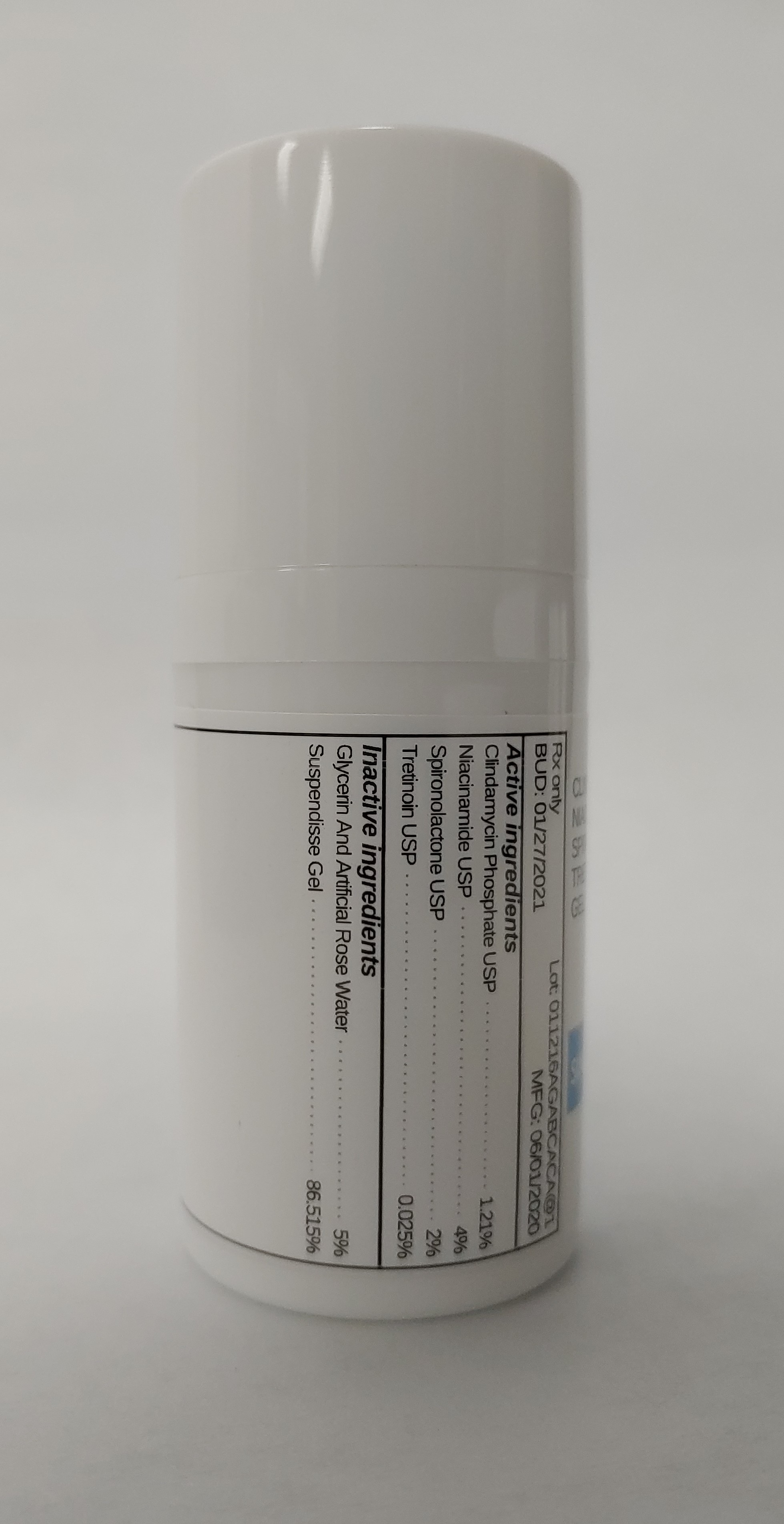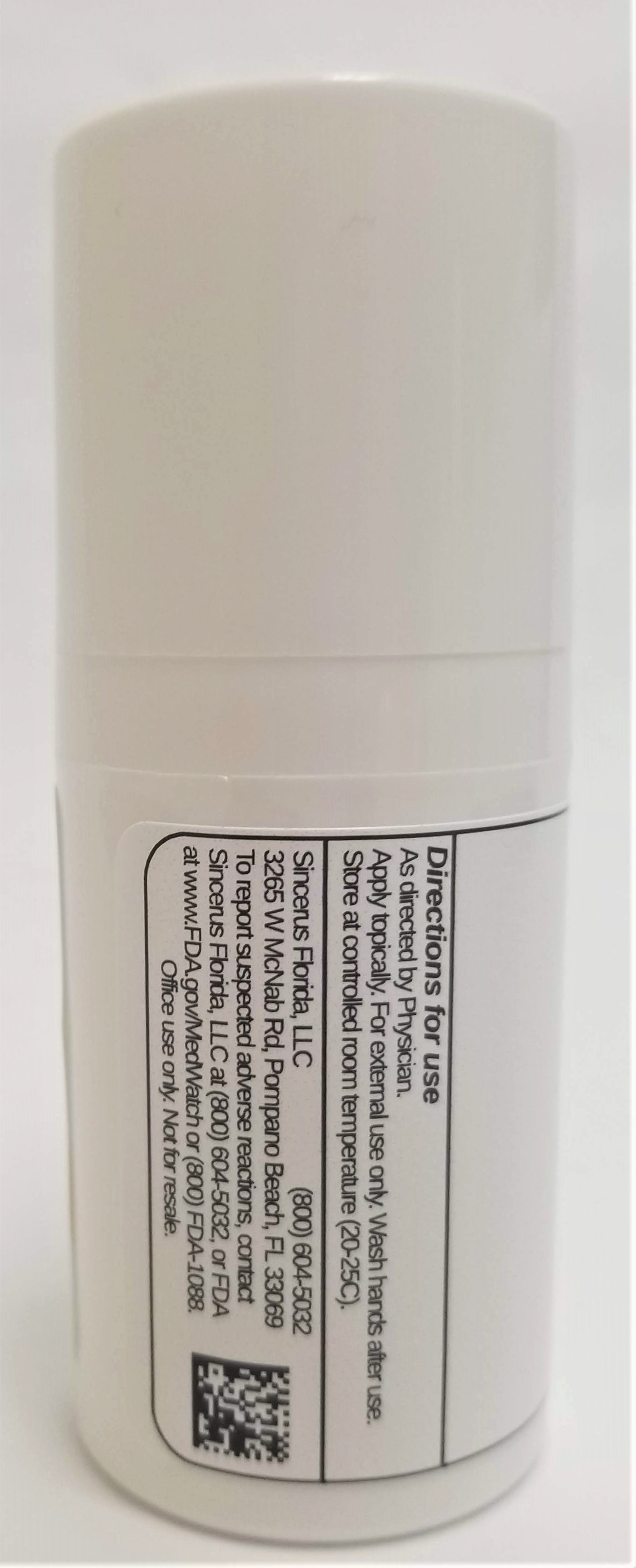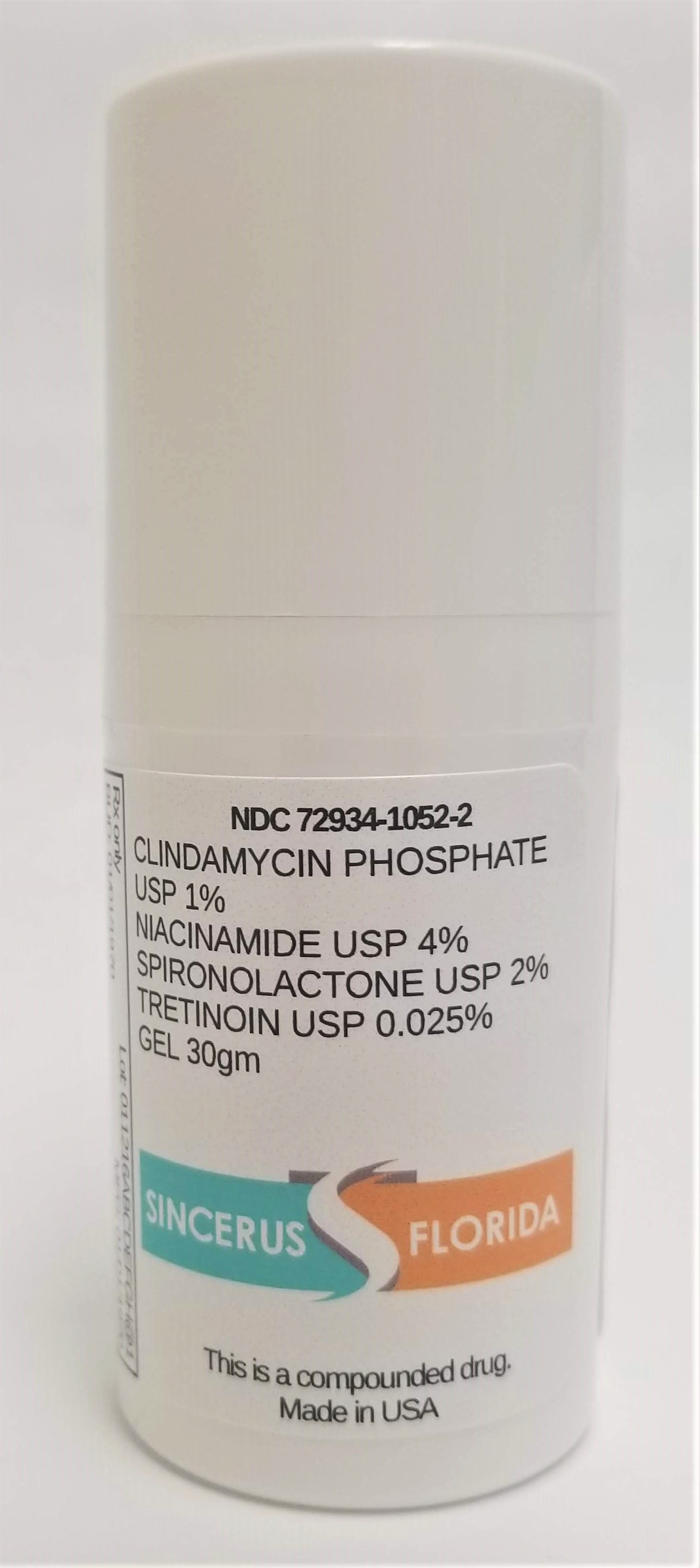 DRUG LABEL: CLINDAMYCIN 1% / NIACINAMIDE 4% / SPIRONOLACTONE 2% / TRETINOIN 0.025%
NDC: 72934-1052 | Form: GEL
Manufacturer: Sincerus Florida, LLC
Category: prescription | Type: HUMAN PRESCRIPTION DRUG LABEL
Date: 20200604

ACTIVE INGREDIENTS: SPIRONOLACTONE 2 g/100 g; TRETINOIN 0.025 g/100 g; CLINDAMYCIN PHOSPHATE 1 g/100 g; NIACINAMIDE 4 g/100 g

CLINDAMYCIN 1% / NIACINAMIDE 4% / SPIRONOLACTONE 2% / TRETINOIN 0.025%